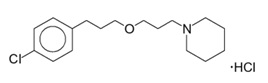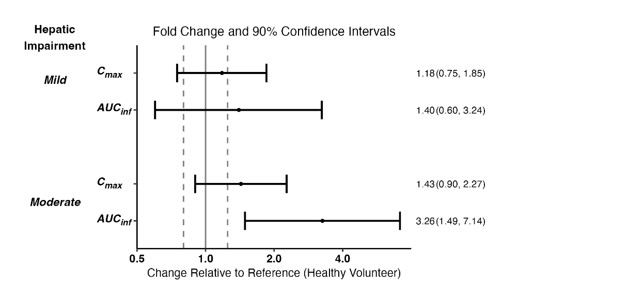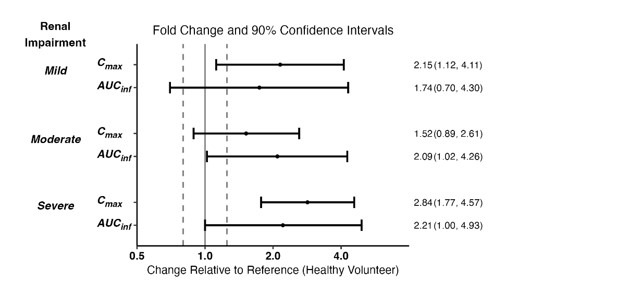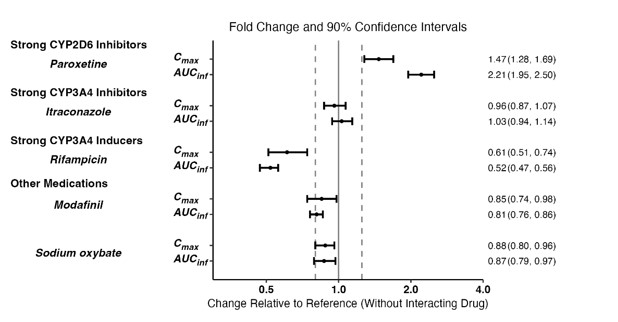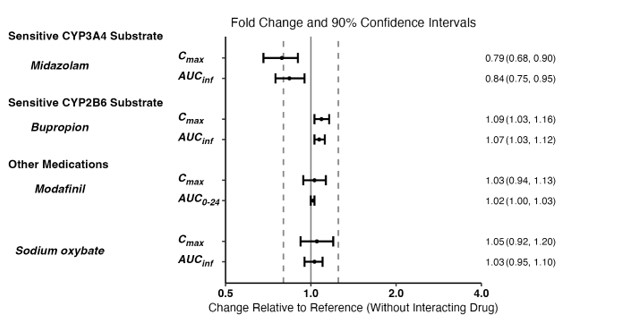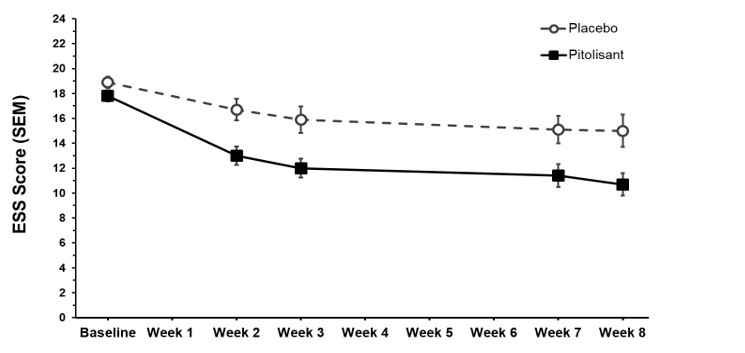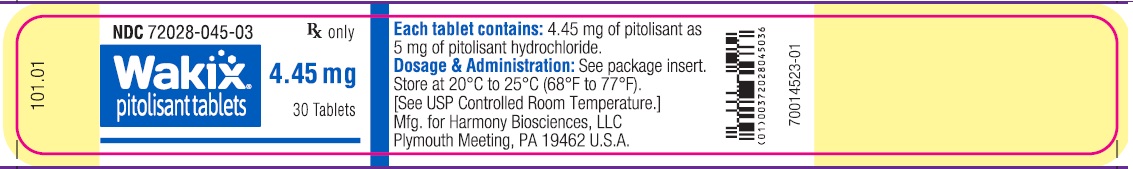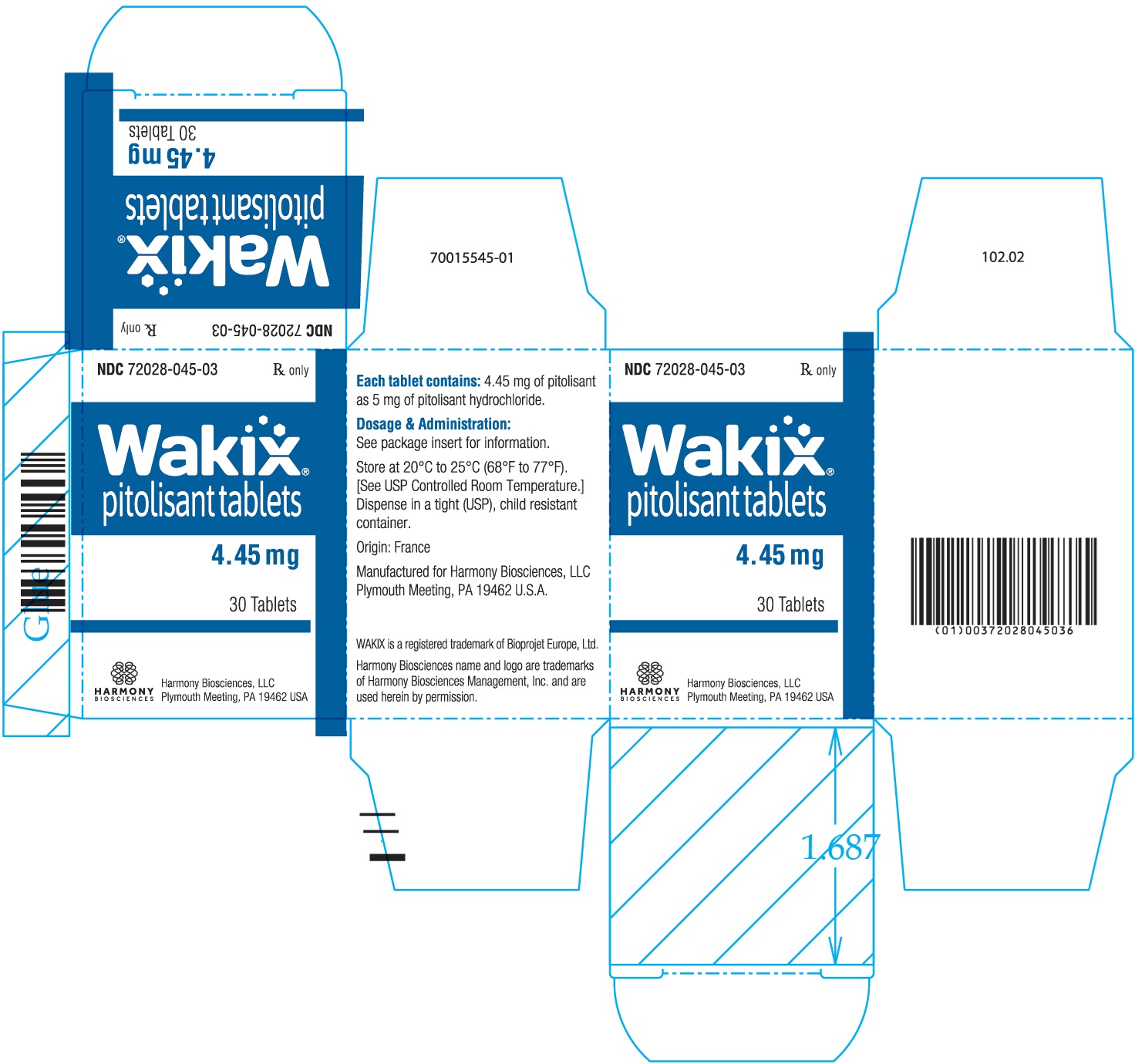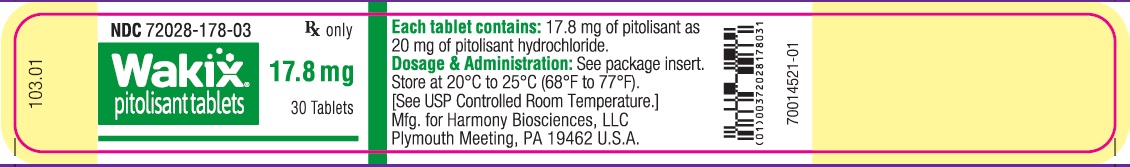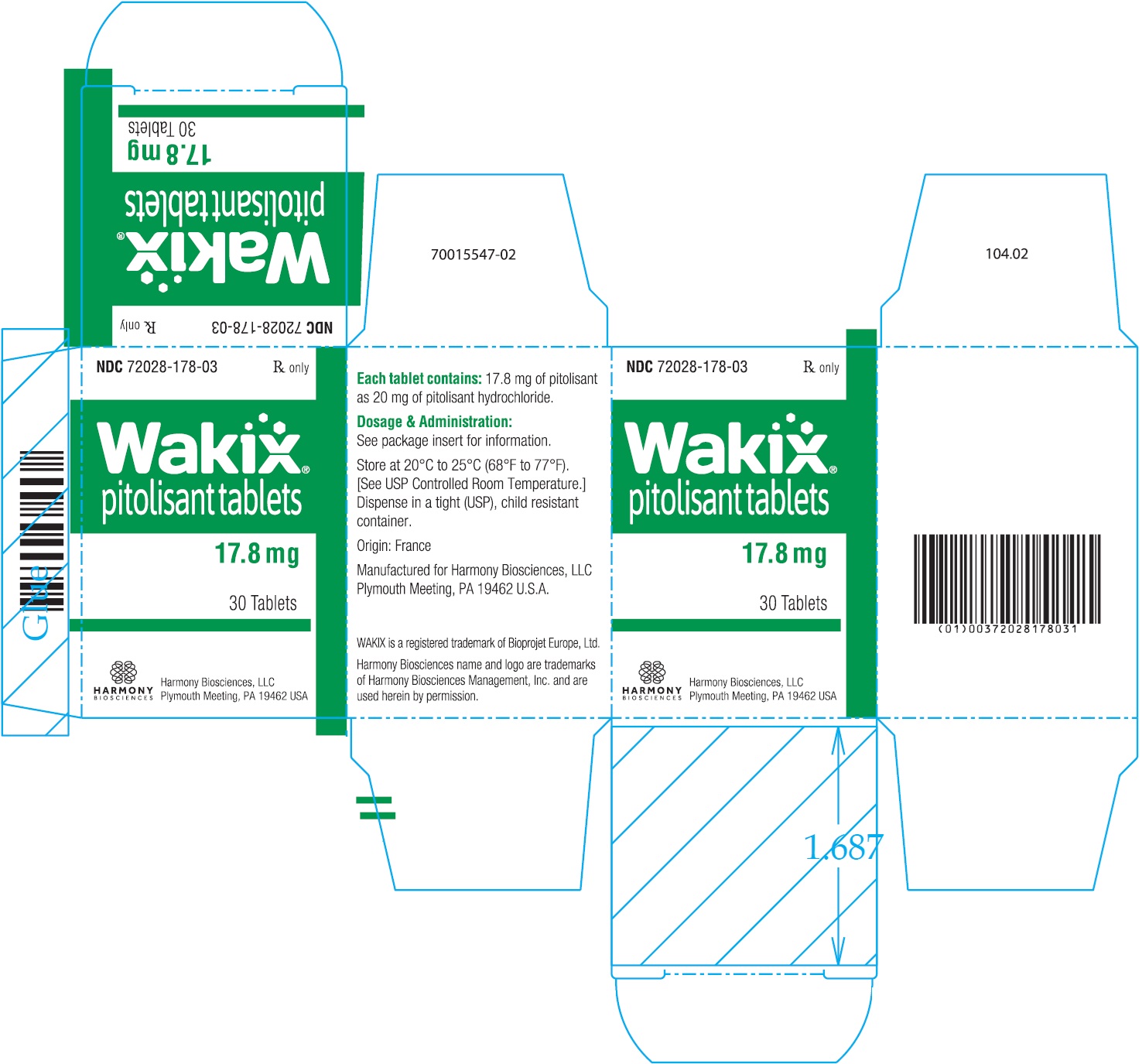 DRUG LABEL: Wakix
NDC: 72028-045 | Form: TABLET, FILM COATED
Manufacturer: Harmony Biosciences, LLC
Category: prescription | Type: HUMAN PRESCRIPTION DRUG LABEL
Date: 20260213

ACTIVE INGREDIENTS: PITOLISANT HYDROCHLORIDE 4.45 mg/1 1
INACTIVE INGREDIENTS: SILICON DIOXIDE; CROSPOVIDONE; MAGNESIUM STEARATE; MICROCRYSTALLINE CELLULOSE; POLYETHYLENE GLYCOL, UNSPECIFIED; POLYVINYL ALCOHOL, UNSPECIFIED; TALC; TITANIUM DIOXIDE

HIGHLIGHTS OF PRESCRIBING INFORMATION

These highlights do not include all the information needed to use WAKIX® safely and effectively. See full prescribing information for WAKIX.
WAKIX® (pitolisant) tablets, for oral use
Initial U.S. Approval: 2019

RECENT MAJOR CHANGES

Indications and Usage (1) | 2/2026
Dosage and Administration (2.1, 2.3) | 2/2026

1 INDICATIONS AND USAGE

WAKIX is a histamine-3 (H3) receptor antagonist/inverse agonist indicated for the treatment of excessive daytime sleepiness (EDS) or cataplexy patients 6 years of age and older with narcolepsy (1)

2 DOSAGE AND ADMINISTRATION

- See Full Prescribing Information for complete dosage instructions (2.2, 2.3)
- Administer orally once daily in the morning upon wakening (2.2, 2.3)
- Dosage Recommendations:

Adults (2.2)
Week 1 | Initiate with a dosage of 8.9 mg once daily
Week 2 | Increase dosage to 17.8 mg once daily
Week 3 | May increase to the maximum recommended dosage of 35.6 mg once daily

Pediatric Patients (6 years and older) (2.3)
Week 1 | Initiate with a dosage of 4.45 mg once daily
Week 2 | Increase dosage to 8.9 mg once daily
Week 3 | Increase dosage to 17.8 mg once daily, the maximum recommended dosage for patients weighing <40 kg
Week 4 | For patients weighing ≥40 kg, may increase to the maximum recommended dosage of 35.6 mg once daily

- Hepatic impairment (2.4, 8.6, 12.3):
  - Moderate hepatic impairment (Child-Pugh Class B):
    Adults: Initial dosage is 8.9 mg once daily. Increase to a maximum dosage of 17.8 mg once daily after 14 days
    Pediatric Patients: Initial dosage is 4.45 mg once daily. Increase to 8.9 mg once daily after 14 days; for patients weighing ≥40 kg, may increase to 17.8 mg once daily after another 14 days
- Renal impairment (eGFR less than 60 mL/minute/1.73 m^2) (2.5, 8.7, 12.3):
  - Adults: Initial dosage is 8.9 mg once daily. Increase to a maximum dosage of 17.8 mg once daily after 7 days
  - Pediatric Patients: Initial dosage is 4.45 mg once daily.Increase to 8.9 mg once daily after 7 days; for patients weighing ≥40 kg, may increase to 17.8 mg once daily after another 7 days
  - End-stage renal disease (ESRD): Not recommended
- Poor Metabolizers of CYP2D6 (2.7):
  - Adults: Maximum recommended dosage is 17.8 mg once daily
  - Pediatric Patients: Maximum recommended dosage is 8.9 mg once daily for patients weighing <40 kg and 17.8 mg for patients weighing ≥40 kg

3 DOSAGE FORMS AND STRENGTHS

Tablets: 4.45 mg and 17.8 mg (3)

4 CONTRAINDICATIONS

- Known hypersensitivity to pitolisant or any component of the formulation (4)
- Severe hepatic impairment (4)

5 WARNINGS AND PRECAUTIONS

QT Interval Prolongation: Increases in QT interval. Avoid use with drugs that also increase the QT interval and in patients with risk factors for prolonged QT interval. Monitor patients with hepatic or renal impairment for increased QTc (5.1)

6 ADVERSE REACTIONS

Most common adverse reactions (≥5% and at least twice placebo) in adults: insomnia, nausea, and anxiety (6.1).

Most common adverse reactions (≥5% and greater than placebo) in pediatric patients 6 years and older: headache and insomnia (6.1).

To report SUSPECTED ADVERSE REACTIONS, contact Harmony Biosciences at 1-800-833-7460 or FDA at 1-800-FDA-1088 or www.fda.gov/medwatch.

7 DRUG INTERACTIONS

- Strong CYP2D6 Inhibitors: Increased exposure of WAKIX; reduce the maximum recommended dose of WAKIX by half (2.6, 7.1)
- Strong CYP3A4 Inducers: Decreased exposure of WAKIX; consider dosage adjustment of WAKIX (2.6, 7.1)
- Sensitive CYP3A4 Substrates (including hormonal contraceptives): WAKIX may reduce effectiveness of sensitive CYP3A4 substrates. Use an alternative non-hormonal contraceptive method during treatment with WAKIX and for at least 21 days after discontinuation of treatment (7.1, 8.3)

FULL PRESCRIBING INFORMATION

1 INDICATIONS AND USAGE

WAKIX is indicated for the treatment of excessive daytime sleepiness (EDS) or cataplexy in patients 6 years of age and older with narcolepsy.

2 DOSAGE AND ADMINISTRATION

2.1 Recommendations Prior to WAKIX Initiation

Consider genotyping patients for CYP2D6 metabolizer status to determine the maximum recommended dosage [see Dosage and Administration (2.7)].

2.2 Recommended Dosage in Adult Patients

The recommended dosage range for WAKIX for the treatment of EDS or cataplexy in adult patients is 17.8 mg to 35.6 mg administered orally once daily in the morning upon wakening.

Titrate dosage as follows:

Week 1: Initiate with a dosage of 8.9 mg (two 4.45 mg tablets) once daily
Week 2: Increase dosage to 17.8 mg (one 17.8 mg tablet) once daily
Week 3: May increase to the maximum recommended dosage of 35.6 mg (two 17.8 mg tablets) once daily

Dose may be adjusted based on tolerability.If a dose is missed, patients should take the next dose the following day in the morning upon wakening.It may take up to 8 weeks for some patients to achieve a clinical response.

2.3 Recommended Dosage in Pediatric Patients 6 Years and Older

The recommended starting dosage of WAKIX for the treatment of EDS or cataplexy in pediatric patients 6 years and older is 4.45 mg administered orally once daily in the morning upon wakening.

Titrate dosage as follows:

Week 1: Initiate with a dosage of 4.45 mg (one 4.45 mg tablet) once daily
Week 2: Increase dosage to 8.9 mg (two 4.45 mg tablets) once daily
Week 3: Increase dosage to 17.8 mg (one 17.8 mg tablet) once daily, which is the maximum recommended dosage for patients weighing <40 kg
Week 4: For patients weighing ≥40 kg, may increase to the maximum recommended dosage of 35.6 mg (two 17.8 mg tablets) once daily

Dose may be adjusted based on tolerability. If a dose is missed, patients should take the next dose the following day in the morning upon wakening. It may take up to 8 weeks for some patients to achieve a clinical response.

2.4 Dosage Recommendations in Patients with Hepatic Impairment

Adult Patients with Moderate (Child-Pugh Class B) Hepatic Impairment

- Initiate WAKIX at 8.9 mg once daily and increase after 14 days to a maximum recommended dosage of 17.8 mg once daily [see Warnings and Precautions (5.1), Use in Specific Populations (8.6), Clinical Pharmacology (12.3)].

Pediatric Patients (6 years and older) with Moderate (Child-Pugh Class B) Hepatic Impairment

- Pediatric patients weighing <40 kg: Initiate WAKIX at 4.45 mg once daily and increase after 14 days to a maximum recommended dosage of 8.9 mg once daily [see Warnings and Precautions (5.1), Use in Specific Populations (8.6), Clinical Pharmacology (12.3)].
- Pediatric patients weighing ≥40 kg: Initiate WAKIX at 4.45 mg once daily and increase after 14 days to 8.9 mg once daily. May increase after another 14 days to a maximum recommended dosage of 17.8 mg once daily [see Warnings and Precautions (5.1), Use in Specific Populations (8.6), Clinical Pharmacology (12.3)].

WAKIX is contraindicated in patients with severe hepatic impairment. WAKIX has not been studied in patients with severe hepatic impairment [see Contraindications (4), Warnings and Precautions (5.1), Use in Specific Populations (8.6), Clinical Pharmacology (12.3)].

2.5 Dosage Recommendations in Patients with Renal Impairment and End-Stage Renal Disease

Adult Patients with eGFR <60 mL/minute/1.73 m^2

- Initiate WAKIX at 8.9 mg once daily and increase after 7 days to a maximum recommended dosage of 17.8 mg once daily [see Warnings and Precautions (5.1), Use in Specific Populations (8.7), Clinical Pharmacology (12.3)].

Pediatric Patients (6 years and older) with eGFR <60 mL/minute/1.73 m^2 (using the Schwartz equation, eGFR (mL/min/1.73 m2)=(0.413*height in cm)/serum creatinine in mg/dL)

- Pediatric patients weighing <40 kg: Initiate WAKIX at 4.45 mg once daily and increase after 7 days to a maximum recommended dosage of 8.9 mg once daily [see Warnings and Precautions (5.1), Use in Specific Populations (8.7), Clinical Pharmacology (12.3)].
- Pediatric patients weighing ≥40 kg: Initiate WAKIX at 4.45 mg once daily and increase after 7 days to 8.9 mg once daily. May increase after another 7 days to a maximum recommended dosage of 17.8 mg once daily [see Warnings and Precautions (5.1), Use in Specific Populations (8.7), Clinical Pharmacology (12.3)].

WAKIX is not recommended in patients with eGFR less than 15 mL/minute/1.73 m^2 [see Warnings and Precautions (5.1), Use in Specific Populations (8.7), Clinical Pharmacology (12.3)].

2.6 Dosage Modifications for Concomitant Use with Strong CYP2D6 Inhibitors and Strong CYP3A4 Inducers

Coadministration with Strong CYP2D6 Inhibitors

- Adult patients: Initiate WAKIX at 8.9 mg once daily and increase after 7 days to a maximum recommended dosage of 17.8 mg once daily [see Drug Interactions (7.1), Clinical Pharmacology (12.3)].
- Pediatric patients (6 years and older) weighing <40 kg: Initiate WAKIX at 4.45 mg once daily and increase after 7 days to a maximum recommended dosage of 8.9 mg once daily [see Drug Interactions (7.1), Clinical Pharmacology (12.3)].
- Pediatric patients (6 years and older) weighing ≥40 kg: Initiate WAKIX at 4.45 mg once daily and increase after 7 days to 8.9 mg once daily. May increase after another 7 days to a maximum recommended dosage of 17.8 mg once daily [see Drug Interactions (7.1), Clinical Pharmacology (12.3)].
- Adult and pediatric patients on a stable dose of WAKIX: Reduce the WAKIX dose by half upon initiating strong CYP2D6 inhibitors [see Drug Interactions (7.1), Clinical Pharmacology (12.3)].

Coadministration with Strong CYP3A4 Inducers

Concomitant use of WAKIX with strong CYP3A4 inducers decreases pitolisant exposure by 50%. Assess for loss of efficacy after initiation of a strong CYP3A4 inducer.

For adult and pediatric patients stable on WAKIX 8.9 mg or 17.8 mg once daily, increase the dose of WAKIX to double the original daily dose (i.e., 17.8 mg or 35.6 mg, respectively) over 7 days.

If concomitant dosing of a strong CYP3A4 inducer is discontinued, decrease WAKIX dosage by half [see Drug Interactions (7.1), Clinical Pharmacology (12.3)].

2.7 Dosage Recommendations in Patients Who Are CYP2D6 Poor Metabolizers

Adult Patients

- Initiate WAKIX at 8.9 mg once daily and increase after 7 days to a maximum recommended dosage of 17.8 mg once daily [see Use in Specific Populations (8.8), Clinical Pharmacology (12.5)].

Pediatric patients

- Pediatric patients (6 years and older) weighing <40 kg: Initiate WAKIX at 4.45 mg once daily and increase after 7 days to a maximum recommended dosage of 8.9 mg once daily [see Use in Specific Populations (8.8), Clinical Pharmacology (12.5)].
- Pediatric patients (6 years and older) weighing ≥40 kg: Initiate WAKIX at 4.45 mg once daily and increase after 7 days to 8.9 mg once daily. May increase after another 7 days to a maximum recommended dosage of 17.8 mg once daily [see Use in Specific Populations (8.8), Clinical Pharmacology (12.5)].

3 DOSAGE FORMS AND STRENGTHS

- WAKIX 4.45 mg tablets: white, round, biconvex film-coated tablet, marked with “S” on one side and plain on the other side. Each tablet contains 5 mg of pitolisant hydrochloride equivalent to 4.45 mg of pitolisant.
- WAKIX 17.8 mg tablets: white, round, biconvex film-coated tablet, marked with “H” on one side and plain on the other side. Each tablet contains 20 mg of pitolisant hydrochloride equivalent to 17.8 mg of pitolisant.

4 CONTRAINDICATIONS

WAKIX is contraindicated in patients with:

- known hypersensitivity to pitolisant or any component of the formulation. Anaphylaxis has been reported in patients treated with WAKIX [see Adverse Reactions (6.2)].
- severe hepatic impairment. WAKIX is extensively metabolized by the liver and there is a significant increase in WAKIX exposure in patients with moderate hepatic impairment [see Use in Specific Populations (8.6)].

5 WARNINGS AND PRECAUTIONS

5.1 QT Interval Prolongation

WAKIX prolongs the QT interval. The use of WAKIX should be avoided in patients with known QT prolongation or in combination with other drugs known to prolong the QT interval [see Drug Interactions (7.1)]. WAKIX should also be avoided in patients with a history of cardiac arrhythmias, as well as other circumstances that may increase the risk of the occurrence of torsade de pointes or sudden death, including symptomatic bradycardia, hypokalemia or hypomagnesemia, and the presence of congenital prolongation of the QT interval [see Clinical Pharmacology (12.2)]. The risk of QT prolongation may be greater in patients with higher concentrations of pitolisant (e.g., patients with hepatic or renal impairment). Monitor patients with hepatic or renal impairment for increased QTc. Dosage modification is recommended in patients with moderate hepatic impairment and moderate or severe renal impairment [see Dosage and Administration (2.4, 2.5)]. WAKIX is contraindicated in patients with severe hepatic impairment [see Contraindications (4)]. WAKIX is not recommended in patients with end-stage renal disease (ESRD) [see Dosage and Administration (2.5), Use in Specific Populations (8.7), Clinical Pharmacology (12.3)].

6 ADVERSE REACTIONS

The following adverse reactions are discussed in more detail in other sections of the labeling:

- QT Interval Prolongation [see Warnings and Precautions (5.1)]

6.1 Clinical Trials Experience

Because clinical trials are conducted under widely varying conditions, adverse reaction rates observed in the clinical trials of a drug cannot be directly compared to rates in the clinical trials of another drug and may not reflect the rates observed in practice.

Adult Patients with Narcolepsy

In clinical trials for narcolepsy, 172 adult patients were treated with WAKIX in placebo-controlled trials for up to 8 weeks and in open-label extension trials for up to 5 years. In trials in which WAKIX was directly compared to placebo, 6 of the 152 patients (3.9%) who received WAKIX and 4 of the 114 patients (3.5%) who received placebo discontinued because of an adverse reaction.

Most Common Adverse Reactions

In the placebo-controlled clinical trials conducted in patients with narcolepsy with or without cataplexy, the most common adverse reactions (occurring in ≥5% of patients and at least twice the rate of placebo) with the use of WAKIX were insomnia (6%), nausea (6%), and anxiety (5%).

Table 1 presents the adverse reactions that occurred at a rate of ≥2% in patients treated with WAKIX and more frequently than in patients treated with placebo in the placebo-controlled clinical trials in narcolepsy.

Table 1: Adverse Reactions that Occurred in ≥2% of WAKIX-Treated Patients and More Frequently than in Placebo-Treated Patients in Three Placebo-Controlled Narcolepsy Studies
Adverse Reaction | WAKIX (n=152) % | Placebo (n=114) %
Headache* | 18 | 15
Insomnia* | 6 | 2
Nausea | 6 | 3
Upper respiratory tract infection* | 5 | 3
Musculoskeletal pain* | 5 | 3
Anxiety* | 5 | 1
Heart rate increased* | 3 | 0
Hallucinations* | 3 | 0
Irritability | 3 | 2
Abdominal pain* | 3 | 1
Sleep disturbance* | 3 | 2
Decreased appetite | 3 | 0
Cataplexy | 2 | 1
Dry mouth | 2 | 1
Rash* | 2 | 1
* The following terms were combined:
Abdominal pain includes: abdominal discomfort; abdominal pain; abdominal pain upper
Anxiety includes: anxiety; nervousness; stress; stress at work
Hallucinations includes: hallucination; hallucination visual; hypnagogic hallucination
Headache includes: cluster headache; headache; migraine; premenstrual headache; tension headache
Heart rate increased includes: heart rate increased; sinus tachycardia; tachycardia
Insomnia includes: initial insomnia; insomnia; middle insomnia; poor quality sleep
Musculoskeletal pain includes: arthralgia; back pain; carpal tunnel syndrome; limb discomfort; musculoskeletal pain; myalgia; neck pain; osteoarthritis; pain in extremity; sciatica
Rash includes: eczema; erythema migrans; rash; urticaria
Sleep disturbance includes: dyssomnia; sleep disorder; sleep paralysis; sleep talking
Upper respiratory tract infection includes: pharyngitis; rhinitis; sinusitis; upper respiratory tract infection; upper respiratory tract inflammation; viral upper respiratory tract infection

Pediatric Patients (6 years and older) with Narcolepsy

In a clinical trial for narcolepsy, 73 pediatric patients 6 years and older were treated with WAKIX in the placebo-controlled phase for up to 8 weeks and 105 patients in the open-label extension phase for up to 8 years.

Most Common Adverse Reactions

In the placebo-controlled phase of the study, the most common adverse reactions (occurring in ≥5% of patients and greater than the rate of placebo) with the use of WAKIX were headache (19%) and insomnia (7%).

The overall adverse reaction profile of WAKIX in the pediatric clinical trial was similar to that seen in the adult clinical trial program.

6.2 Postmarketing Experience

The following adverse reactions have been identified during post-approval use of WAKIX. Because these reactions are reported voluntarily from a population of uncertain size, it is not always possible to reliably estimate their frequency or establish a causal relationship to drug exposure:

General disorders and administration site conditions: fatigue

Immune system disorders: hypersensitivity (anaphylaxis)

Investigations: weight increased

Nervous system disorders: dizziness, epilepsy

Psychiatric disorders: abnormal behavior, abnormal dreams, anhedonia, bipolar disorder, depression, depressed mood, nightmare, sleep disorder, suicide attempt, suicidal ideation

Skin and subcutaneous tissue disorders: pruritus

7 DRUG INTERACTIONS

7.1 Drugs Having Clinically Important Interactions with WAKIX

Table 2: Clinically Significant Drug Interactions with WAKIX
Effect of Other Drugs on WAKIX
Strong CYP2D6 Inhibitors
Clinical Implication: | Concomitant administration of WAKIX with strong CYP2D6 inhibitors increases pitolisant exposure by 2.2-fold.
Prevention or Management: | Reduce the dose of WAKIX by half [see see Dosage and Administration (2.6), Clinical Pharmacology (12.3)].
Strong CYP3A4 Inducers
Clinical Implication: | Concomitant use of WAKIX with strong CYP3A4 inducers decreases exposure of pitolisant by 50%.
Prevention or Management: | Assess for loss of efficacy after initiation of a strong CYP3A4 inducer. For patients stable on WAKIX 8.9 mg or 17.8 mg once daily, increase the dose of WAKIX to reach double the original daily dose (i.e., 17.8 mg or 35.6 mg, respectively) over 7 days. If concomitant dosing of a strong CYP3A4 inducer is discontinued, decrease WAKIX dosage by half [see see Dosage and Administration (2.6), Clinical Pharmacology (12.3)].
Histamine-1 (H1) Receptor Antagonists
Clinical Implication: | WAKIX increases the levels of histamine in the brain; therefore, H1 receptor antagonists that cross the blood-brain barrier may reduce the effectiveness of WAKIX.
Prevention or Management: | Avoid centrally acting H1 receptor antagonists.
QT Interval Prolongation
Clinical Implication: | Concomitant use of drugs that prolong the QT interval may add to the QT effects of WAKIX and increase the risk of cardiac arrhythmia.
Prevention or Management: | Avoid the use of WAKIX in combination with other drugs known to prolong the QT interval [see Warnings and Precautions (5.1)].
Effect of WAKIX on Other Drugs
Sensitive CYP3A4 Substrates
Clinical Implication: | WAKIX is a borderline/weak inducer of CYP3A4. Therefore, reduced effectiveness of sensitive CYP3A4 substrates may occur when used concomitantly with WAKIX [see Clinical Pharmacology (12.3)]. The effectiveness of hormonal contraceptives (e.g., ethinyl estradiol) may be reduced when used with WAKIX and effectiveness may be reduced for 21 days after discontinuation of therapy.
Prevention or Management: | Patients using hormonal contraception should be advised to use an alternative non-hormonal contraceptive method during treatment with WAKIX and for at least 21 days after discontinuation of treatment [see Use in Specific Populations (8.3)].

8 USE IN SPECIFIC POPULATIONS

8.1 Pregnancy

Pregnancy Exposure Registry

There is a pregnancy exposure registry that monitors pregnancy outcomes in women who are exposed to WAKIX during pregnancy. Patients should be encouraged to enroll in the WAKIX pregnancy registry if they become pregnant. To enroll or obtain information from the registry, patients can call 1-800-833-7460.

Risk Summary

Available case reports from clinical trials and postmarketing reports with WAKIX use in pregnant women have not determined a drug-associated risk of major birth defects, miscarriage or adverse maternal or fetal outcomes. In animal reproductive studies, administration of pitolisant during organogenesis caused maternal and embryofetal toxicity in rats and rabbits at doses ≥13 and >4 times the maximum recommended human dose (MRHD) of 35.6 mg based on mg/m^2 body surface area, respectively. Oral administration of pitolisant to female rats during pregnancy and lactation adversely affected maternal and fetal health and produced developmental delay at doses ≥13 times the MRHD, based on mg/m^2 body surface area and increased the incidence of major malformations at 22 times the MRHD (see Data).

The estimated background risk of major birth defects and miscarriage for the indicated population is unknown. All pregnancies have a background risk of birth defect, loss, or other adverse outcomes. In the U.S. general population, the estimated background risk of major birth defects and miscarriage in clinically recognized pregnancies is 2% to 4% and 15% to 20%, respectively.

Data

Animal Data

Pitolisant was administered orally to pregnant rats during the period of organogenesis at doses of 30, 52, 90 and 110 mg/kg/day, which are approximately 7, 13, 22 and 27 times the MRHD, based on mg/m2 body surface area, respectively. Maternal toxicity occurred at >22 times the MRHD and included convulsions and decreases in body weight and food consumption. At these maternally toxic doses, no adverse effects on embryofetal development were noted and the no observed-adverse-effect-level for embryofetal toxicity is 27 times the MRHD based on mg/m^2 body surface area.

Pitolisant was administered intramuscularly to pregnant rabbits during the period of organogenesis at doses of 4, 8, and 16 mg/kg/day, which are approximately 2, 4 and 8 times the MRHD, based on mg/m^2 body surface area, respectively. Maternal toxicity occurred at ≥4 times the MRHD and included significant body weight loss and decreased food consumption. Mortality (1 animal) and convulsions (2 animals) occurred at 8 times the MRHD. At the maternally toxic dose (8 times the MRHD), the incidence of pre-implantation loss and abortions increased with a consequent decrease in both the number of implantations and live fetuses. Pitolisant was not teratogenic at doses up to 8 times the MRHD; however, delayed skeletal development (incomplete ossification and supernumerary ribs) was observed. The no-observed-adverse-effect-level for maternal toxicity and embryofetal development is 2 and 4 times the MRHD based on mg/m^2 body surface area, respectively.

Pitolisant was administered orally to pregnant rats from gestation day 7 through lactation day 20 post-partum at doses of 30, 52, and 90 mg/kg/day, which are 7, 13 and 22 times the MRHD, based on mg/m^2 body surface area, respectively. Maternal toxicity included death, CNS signs including convulsions, and significant decrease in body weight and food consumption at 22 times the MRHD based on mg/m^2 body surface area. At the maternally toxic dose (22 times the MRHD), fetal toxicity included stillbirths, postnatal pup mortality (due to lack of milk and/or failure to nurse), and decreased pup length and weight. A single female at the mid dose (13 times the MRHD) also failed to produce milk resulting in pup mortality. At the maternally toxic dose (22 times the MRHD), pitolisant was teratogenic causing major malformations (cleft palate, abnormal limb flexure). F1 toxicity included delay in postnatal development (decrease in body weight and length, delay in incisor eruption, and delay in testes descent), which occurred at ≥13 times the MRHD; however, there was no effect on sexual maturation or reproductive capacity of the F1 generation. The no-observed-adverse-effect-level for developmental toxicity is approximately 7 times the MRHD, based on mg/m^2 body surface area.

8.2 Lactation

Risk Summary

The transfer of pitolisant into breastmilk is low based on data from a lactation study. The mean infant dose was 0.009 mg/day, and the relative infant dose was less than 1% of the maternal weight-adjusted dose (see Data). There are no data on the effects of pitolisant on the breastfed infant, or the effect of this drug on milk production.

The developmental and health benefits of breastfeeding should be considered along with the mother’s clinical need for WAKIX and any potential adverse effects on the breastfed infant from WAKIX or from the underlying maternal condition.

Data

An open-label study in 8 healthy lactating women who were 11 to 96 weeks post-partum evaluated the concentration of pitolisant in breast milk samples collected over 24 hours and serum samples collected over 120 hours after a single dose administration of 35.6 mg of pitolisant. Pitolisant was present in breast milk with a mean Cmax of 47.5 ng/mL, while the mean Cmax of pitolisant in serum was 61.4 ng/mL. Following a single dose of pitolisant 35.6 mg, approximately 50% of the amount of pitolisant measured in breast milk occurred during the first 4 hours post dose. Based on single dose data, the mean infant dosage of pitolisant was calculated to be 0.009 mg/day, which represented a mean of 0.564% of the maternal dose received.

8.3 Females and Males of Reproductive Potential

Contraception

WAKIX may reduce the effectiveness of hormonal contraceptives. Patients using hormonal contraception should be advised to use an alternative non-hormonal contraceptive method during treatment with WAKIX and for at least 21 days after discontinuing treatment [see Drug interactions (7.1), Clinical Pharmacology (12.3)].

8.4 Pediatric Use

The safety and effectiveness of WAKIX have been established for the treatment of excessive daytime sleepiness or cataplexy in pediatric patients 6 years of age and older with narcolepsy. Use of WAKIX in this age group is supported by one adequate and well-controlled study in 110 pediatric patients with narcolepsy ages 6 to less than 18 years of age [see Clinical Studies (14.1)].

The safety and effectiveness of WAKIX have not been established for the treatment of excessive daytime sleepiness or cataplexy in pediatric patients less than 6 years of age with narcolepsy.

Juvenile Animal Toxicity Data

In a juvenile animal study, male and female rats were administered pitolisant at 9, 21, or 48 mg/kg/day by oral gavage from postnatal day (PND) 7 to PND 70. Mortality occurred at the highest dose of 48 mg/kg/day; however, death was primarily related to aspiration/inhalation of food material. No adverse effects on growth and development up to the high dose were observed; however, plasma exposures at this dose were lower than those predicted to occur in pediatric patients at the maximum recommended human dose (MRHD) of 35.6 mg due to low oral bioavailability in juvenile rats.

In a second juvenile animal study, male and female rats were administered pitolisant at 15 or 30 mg/kg/day or 30 mg/kg/twice daily (60 mg/kg/day) by intraperitoneal injection from PND 7 to PND 70. Mortality and convulsions were observed at the top two doses of 30 and 60 mg/kg/day. Similar findings of convulsions and mortality were also observed in studies in adult rats at comparable doses. The no-observed-adverse-effect-level (NOAEL) is 15 mg/kg/day in juvenile animals administered pitolisant by intraperitoneal injection, which corresponds to plasma exposures that are approximately 4 times and 1 times the predicted pediatric exposures at the MRHD of 35.6 mg, based on Cmax and AUC, respectively.

8.5 Geriatric Use

Limited pharmacokinetic data are available in healthy elderly subjects. A pharmacokinetic study that compared 12 elderly subjects (age 68 to 82 years) to 12 healthy adults (age 18 to 45 years) did not reveal any significant differences in drug exposure [see Clinical Pharmacology (12.3)].

Of the total number of adult patients with narcolepsy in clinical studies of WAKIX, 14 patients (5%) were ≥65 years old. No overall differences in safety or effectiveness were observed between these patients and younger patients in these clinical trials, but greater sensitivity of some older individuals cannot be ruled out. In general, dose selection for an elderly patient should be cautious, usually starting at the low end of the dosing range, reflecting the greater frequency of decreased hepatic, renal, and cardiac function, concomitant diseases, and other drug therapy.

8.6 Hepatic Impairment

WAKIX is contraindicated in patients with severe hepatic impairment (Child-Pugh Class C) as it has not been studied in this population. WAKIX is extensively metabolized by the liver and there is a significant increase in WAKIX exposure in patients with moderate hepatic impairment [see Contraindications (4), Clinical Pharmacology (12.3)].

Monitor patients with moderate hepatic impairment (Child-Pugh Class B) and adjust the dosage of WAKIX [see Dosage and Administration (2.4)].

Monitor patients with mild hepatic impairment (Child-Pugh Class A). No dosage adjustment of WAKIX is recommended in patients with mild hepatic impairment.

8.7 Renal Impairment

The pharmacokinetics of WAKIX in patients with end-stage renal disease (ESRD) (eGFR of <15 mL/minute/1.73 m^2) is unknown [see Clinical Pharmacology (12.3)]. Therefore, WAKIX is not recommended in patients with ESRD [see Dosage and Administration (2.5), Warnings and Precautions (5.1)].

Dosage adjustment of WAKIX is recommended in patients with eGFR <60 mL/minute/1.73 m^2 [see Dosage and Administration (2.5)].

8.8 Use in Genomic Subgroups

The maximum recommended dosage is lower in patients who are CYP2D6 poor metabolizers because these patients have higher pitolisant concentrations than CYP2D6 normal metabolizers and may have increased risk of adverse events [see Dosage and Administration (2.7), Warnings and Precautions (5.1), Clinical Pharmacology 12.5)].

The prevalence of CYP2D6 poor metabolizers is approximately 7% in White populations, 2% in Asian populations, and 2% in Black or African American populations.

10 OVERDOSAGE

Human Experience

In premarketing clinical studies, overdosage of WAKIX was identified in one patient who ingested 320.4 mg of WAKIX (9 times the maximum recommended daily dose). The patient experienced nystagmus and twitching, reported generalized pain, and had QT prolongation. The patient was monitored in the hospital, received supportive care, and was discharged the following day without sequelae.

There have been postmarketing reports of overdoses of WAKIX. The most frequently reported symptoms with overdoses up to 71.2 mg (twice the maximum recommended daily dose) were headache, nausea, and hallucinations.

Management of Overdosage

No specific antidote for WAKIX is known. In managing acute overdosage, provide general symptomatic and supportive care including close medical supervision and monitoring of vital signs and cardiac rhythm. Specifically, continuous cardiovascular monitoring should be initiated to detect possible arrhythmias [see Warnings and Precautions (5.1)]. Consider contacting the Poison Help line (1-800-222-1222) or a medical toxicologist for additional overdose management recommendations.

11 DESCRIPTION

WAKIX tablets contain pitolisant hydrochloride. Pitolisant is an antagonist/inverse agonist of the histamine-3 (H3) receptor. Pitolisant hydrochloride is a white or almost white crystalline powder with a molecular formula of C17H26ClNO·HCl and a molecular weight of 332.31. Pitolisant hydrochloride is soluble in water, ethanol, and methylene chloride and practically insoluble in cyclohexane. The chemical name of pitolisant hydrochloride is 1-{3-[3-(4-chlorophenyl)propoxy]propyl}piperidine, hydrochloride and its structural formula is:

The molecular formula of the pitolisant free base is C17H26ClNO and its molecular weight is 295.85.

WAKIX tablets are for oral administration and each film-coated tablet contains 5 mg or 20 mg of pitolisant hydrochloride (equivalent to 4.45 mg or 17.8 mg of pitolisant free base, respectively) and the following inactive ingredients: colloidal silicon dioxide, crospovidone, magnesium stearate, microcrystalline cellulose, polyethylene glycol, polyvinyl alcohol, talc, and titanium dioxide.

12 CLINICAL PHARMACOLOGY

12.1 Mechanism of Action

The mechanism of action of pitolisant in excessive daytime sleepiness (EDS) or cataplexy in patients 6 years and older with narcolepsy is unclear. However, its efficacy could be mediated through its activity as an antagonist/inverse agonist at histamine-3 (H3) receptors.

12.2 Pharmacodynamics

Pitolisant binds to H3 receptors with a high affinity (Ki = 1 nM) and has no appreciable binding to other histamine receptors (H1, H2, or H4 receptors; Ki ≥10 µM).

Cardiac Electrophysiology

WAKIX at the highest recommended dosage (i.e., 35.6 mg daily) led to a QTc increase of 4.2 msec. Exposures 3.8-fold higher than achieved at the highest recommended dose increased QTc 16 msec (mean) [see Warnings and Precautions (5.1)].

12.3 Pharmacokinetics

Following oral administration of pitolisant 35.6 mg once daily, the steady state Cmax and AUC are 73 ng/mL (range: 49.2 to 126 ng/mL) and 812 ng*hr/mL (range: 518 to 1468 ng*hr/mL), respectively. Pitolisant exposure (Cmax and AUC) increases proportionally with dose and steady state is reached by day 7.

Absorption

The median time to maximum plasma concentration (Tmax) of pitolisant is 3.5 hours (2 to 5 hours).
The oral absorption of WAKIX is around 90%.

Food Effect

No clinically significant differences in the pharmacokinetics of pitolisant were observed following administration with a high-fat meal (approximately 950 calories, 62% fat).

Distribution

The apparent volume of distribution of pitolisant is approximately 700 L (5 to 10 L/kg). Serum protein binding is approximately 91% to 96%. The blood to plasma ratio of pitolisant is 0.55 to 0.89.

Elimination

After a single dose of 35.6 mg, the median half-life of pitolisant is approximately 20 hours (7.5 to 24.2 hours). The apparent oral clearance (CL/F) of pitolisant is 43.9 L/hr and renal clearance accounts for <2% of the total clearance of pitolisant.

Metabolism

Pitolisant is primarily metabolized by CYP2D6 and to a lesser extent by CYP3A4; these metabolites are further metabolized or conjugated with glycine or glucuronic acid. None of these metabolites are pharmacologically active.

Excretion

After a single oral radiolabeled pitolisant 17.8 mg dose, approximately 90% of the dose was excreted in urine (<2% unchanged) and 2.3% in feces.

Specific Populations

No clinically significant differences in the pharmacokinetics of pitolisant were observed based on age (18 to 82 years old), sex, race/ethnicity (Caucasians or Blacks), or body weight (48 to 103 kg). The effects of end-stage renal disease and severe hepatic impairment on the pharmacokinetics of pitolisant are unknown.

Pediatric Patients

Pharmacokinetic data from 24 pediatric patients with narcolepsy (ages 7 to 17 years) receiving a single dose of WAKIX suggest that pediatric patients have higher exposure to pitolisant than adults. The geometric mean Cmax and AUC0-10h of pitolisant were 2.2 and 2.0-fold higher, respectively, in pediatric patients 12 to 17 years and 3.4 and 3.6-fold higher, respectively, in pediatric patients 7 to 11 years compared to adults.

Patients with Hepatic Impairment

Six subjects with mild hepatic impairment (Child-Pugh Class A), 6 subjects with moderate hepatic impairment (Child-Pugh Class B), and 12 healthy subjects matched for age, sex, body mass index and ethnicity received a single dose of WAKIX 17.8 mg to assess the pharmacokinetics of WAKIX in patients with hepatic impairment. Exposure of pitolisant in patients with mild or moderate hepatic impairment is summarized in Figure 1. No studies have been conducted in patients with severe hepatic impairment.

Figure 1: Effect of Hepatic Impairment on Pitolisant Pharmacokinetics

Dots = Geometric least squares mean ratios, Error bars = 90% CI; reference dashed lines are 0.8 and 1.25.
AUCinf = area under the curve from time 0 to time infinity; Cmax = maximum plasma concentration.

Patients with Renal Impairment

A single dose of WAKIX 17.8 mg was administered to 4 subjects with mild renal impairment (eGFR of 60 to 89 mL/min/1.73 m^2), 4 subjects with moderate renal impairment (eGFR of 30 to 59 mL/min/1.73 m^2), 4 subjects with severe renal impairment (eGFR of 15 to 29 mL/min/1.73 m^2), and 12 subjects with normal renal function (i.e., eGFR >90 mL/min/1.73 m^2) to assess the pharmacokinetics of WAKIX in patients with renal impairment. Exposure of pitolisant in patients with mild, moderate, and severe renal impairment is summarized in Figure 2. No studies have been conducted in patients with ESRD.

Figure 2: Effect of Renal Impairment on Pitolisant Pharmacokinetics

Dots = Geometric least squares mean ratios, Error bars = 90% CI; reference dashed lines are 0.8 and 1.25.
AUCinf = area under the curve from time 0 to time infinity; Cmax = maximum plasma concentration.

Drug-Drug Interactions

Effect of Other Drugs on the Pharmacokinetics of WAKIX

The effect of pitolisant on the pharmacokinetics of other drugs is presented in Figure 3 [see Dosage and Administration (2.6, Drug Interactions (7.1)].

Figure 3: Effect of Concomitant Medications on Pitolisant

Dots = Geometric least squares mean ratios, Error bars = 90% CI; reference dashed lines are 0.8 and 1.25.
AUCinf = area under the curve from time 0 to time infinity; Cmax = maximum plasma concentration.

Effect of WAKIX on the Pharmacokinetics of Other Drugs

The effect of pitolisant on the pharmacokinetics of other drugs is presented in Figure 4 [see Drug Interactions (7.1), Use in Specific Populations (8.3)].

Figure 4: Effect of Pitolisant on Concomitant Medications

Dots = Geometric least squares mean ratios, Error bars = 90% CI; reference dashed lines are 0.8 and 1.25.
AUCinf = area under the curve from time 0 to time infinity; AUC0-24 = area under the curve from time 0 to 24 hours; Cmax = maximum plasma concentration.

12.5 Pharmacogenomics

Pitolisant is metabolized by CYP2D6 [see Clinical Pharmacology (12.3)]. The gene encoding CYP2D6 has variants that affect CYP2D6 metabolic function. CYP2D6 poor metabolizers are individuals with two nonfunctional alleles (e.g., CYP2D6*5/*5), and as a result have no CYP2D6 enzyme activity.

Administration of WAKIX 17.8 mg daily for 7 days resulted in 2.4 times higher AUC and 2.1 times higher Cmax in CYP2D6 poor metabolizers (n=3) compared to CYP2D6 normal metabolizers (n=5). [see Dosage and Administration (2.7), Use in Genomic Subgroups (8.8)].

13 NONCLINICAL TOXICOLOGY

13.1 Carcinogenesis, Mutagenesis, Impairment of Fertility

Carcinogenesis

Pitolisant was not carcinogenic in mice or rats.

Oral administration of pitolisant at 15, 30, and 75 mg/kg/day for 6 months to CB6F1 TgrasH2 transgenic mice did not increase tumor incidence. These doses are 2, 4, and 9 times the MRHD, respectively, based on mg/m^2 body surface area.

Oral administration of pitolisant at 5, 15, and 30 mg/kg/day for 105 weeks to Sprague-Dawley rats did not increase tumor incidence. These doses are 1.4, 4, and 8 times the MRHD based on mg/m^2 body surface area.

Mutagenesis

Pitolisant and its metabolites were not mutagenic in the in vitro bacterial reverse mutation assay (Ames), or clastogenic in the in vitro mammalian chromosomal aberration assay. Pitolisant was negative in the in vivo mouse micronucleus assay.

Impairment of Fertility

Oral administration of pitolisant at 30, 52, and 90 mg/kg/day to male and female rats prior to and throughout mating and continuing in females through early gestation resulted in adverse effects at the mid and high doses. These doses are 13 and 22 times the MRHD, respectively, based on mg/m^2 body surface area (BSA). A dose-related increase in the percentage of post-implantation loss was observed compared to controls, leading to a decrease in the percentage of live conceptuses, at doses 13 and 22 times the MRHD, based on mg/m^2 BSA. Pitolisant caused dose-related abnormalities in sperm morphology and decreased motility at doses that are 13 and 22 times the MRHD based on mg/m^2 BSA, without any significant effects on fertility indices in male rats. No effects on fertility were observed at 30 mg/kg/day (7 times the MRHD based on mg/m^2 BSA).

13.2 Animal Toxicology and/or Pharmacology

Adverse CNS-related clinical signs including tremors and convulsions occurred after single and repeated oral administration of pitolisant across multiple species. In a 9-month repeat-dose toxicity study in adult monkeys, sporadic incidences of convulsions occurred at doses corresponding to exposures approximately 3 times the MRHD based on Cmax and 1 times the MRHD, based on AUC. Convulsions were first observed close to Tmax and resolved by 2 hours after dosing. Convulsions were not observed after discontinuation of dosing and were not associated with microscopic findings in the brain. Safety margins at the no-observed-adverse-effect-level (NOAEL) correspond to 1 times the MRHD based on Cmax and 0.4 times based on AUC.

14 CLINICAL STUDIES

14.1 Excessive Daytime Sleepiness (EDS) in Patients with Narcolepsy

Adult Patients with Narcolepsy

The efficacy of WAKIX for the treatment of excessive daytime sleepiness in adult patients with narcolepsy was evaluated in two multicenter, randomized, double-blind, placebo-controlled studies (Study 1; NCT01067222 and Study 2; NCT01638403). Patients ≥18 years of age who met the International Classification of Sleep Disorders (ICSD-2) criteria for narcolepsy (with or without cataplexy) and who had an Epworth Sleepiness Scale (ESS) score ≥14 were eligible to enroll in the studies. EDS was assessed using the ESS, an 8-item questionnaire by which patients rate their perceived likelihood of falling asleep during usual daily life activities. Each of the 8 items on the ESS is rated from 0 (would never doze) to 3 (high chance of dozing); the maximum score is 24. Study 1 and Study 2 included an 8-week treatment period: a 3-week dose titration phase followed by a 5-week stable dose phase. These studies compared WAKIX to both a placebo and an active control.

In Study 1, 95 patients were randomized to receive WAKIX, placebo, or active control. The dose of WAKIX was initiated at 8.9 mg once daily and could be increased at weekly intervals to 17.8 mg or 35.6 mg, based on clinical response and tolerability. No dose adjustments were permitted during the 5-week stable dose phase. 61% of patients reached a stable dose of 35.6 mg. Median age in the study was 37 years. More than 90% of patients in the WAKIX and placebo groups were Caucasian and 54% were male. Approximately 80% of the population had a history of cataplexy.

WAKIX demonstrated statistically significantly greater improvement on the primary endpoint, the least squares mean final ESS score compared to placebo (Table 3).

In Study 2, 166 patients were randomized to receive WAKIX, placebo, or active control. The dose of WAKIX was initiated at 4.45 mg and could be increased at weekly intervals to 8.9 mg or 17.8 mg, based on clinical response and tolerability. No dose adjustments were permitted during the 5-week stable-dose phase. 76% of patients reached a stable dose of 17.8 mg. Median age in the study was 40 years. In the WAKIX and placebo groups, approximately 50% of patients were male, 90% of patients were Caucasian, and 75% of patients had a history of cataplexy.

WAKIX demonstrated statistically significantly greater improvement on the primary endpoint, the least squares mean final ESS score compared to placebo (Table 3).

Examination of demographic subgroups by sex did not suggest differences in response.

The efficacy results from Study 1 and Study 2 are shown in Table 3.

Table 3: Efficacy Results for Epworth Sleepiness Scale in Adult Patients with Narcolepsy (Study 1 and Study 2)
Study | Treatment Group (N) | Baseline ESS Score Mean (SD) | Final ESS Scorec LS Mean at Week 8 (SE) | Placebo Subtracted Difference [95% CI] at Week 8d
Study 1a | WAKIX (n=31) | 17.8 (2.5) | 12.4 (1.01) | -3.1 [-5.73; -0.46]
Study 1a | Placebo (n=30) | 18.9 (2.5) | 15.5 (1.03) | -3.1 [-5.73; -0.46]
Study 2b | WAKIX (n=66) | 18.3 (2.4) | 13.3 (1.19) | -2.2 [-4.17; -0.22]
Study 2b | Placebo (n=32) | 18.2 (2.3) | 15.5 (1.32) | -2.2 [-4.17; -0.22]
CI = confidence interval; LS Mean = least squares mean; SD = standard deviation; SE = standard error
aMaximum dose randomized to was 35.6 mg
bMaximum dose randomized to was 17.8 mg
cA lower score on the ESS represents improvement; scores range from 0 (no symptoms) to 24 (worst symptoms)
dA negative value for the placebo subtracted difference represents improvement

Figure 5 shows the ESS score from baseline to Week 8 in Study 1.

Figure 5: Epworth Sleepiness Scale Score (mean ± SEM) from Baseline to Week 8 in Study 1

SEM = standard error of the mean (raw mean scores)
ESS scores range from 0 to 24, with 0 being the best score and 24 being the worst score

Pediatric Patients (6 years of age and older) with Narcolepsy

The efficacy of WAKIX for the treatment of excessive daytime sleepiness in pediatric patients 6 years of age and older with narcolepsy was evaluated in one multicenter, randomized, double-blind, placebo-controlled study (Study 4; NCT02611687). Pediatric patients 6 to 17 years who met the International Classification of Sleep Disorders (ICSD-3) criteria for narcolepsy (with or without cataplexy) and who had a Pediatric Daytime Sleepiness Scale (PDSS) score ≥15 were eligible to enroll in the study. EDS was assessed with the PDSS, an 8-item questionnaire in which patients report their frequency of EDS-related symptoms. Each of the 8 items on the PDSS is rated from 0 (never) to 4 (very often, always); the maximum score is 32, with higher scores representing greater severity of symptoms. The study included an 8-week treatment period: a 4-week dose titration phase followed by a 4-week stable dose phase.

In Study 4, 110 pediatric patients 6 to 17 years were randomized to receive WAKIX or placebo. The dose of WAKIX was initiated at 4.45 mg once daily and could be increased at weekly intervals to 17.8 mg for patients weighing <40 kg or 35.6 mg for patients weighing≥40 kg, based on clinical response and tolerability. No dose adjustments were permitted during the 4-week stable dose phase. 69% of patients weighing <40 kg reached a stable dose of 17.8 mg and 72% of patients weighing ≥40 kg reached a stable dose of 35.6 mg. Median age in the study was 13 years, 56% of the patients were male, and 86% of the population had a history of cataplexy. Race and ethnicity were not collected in this study.

WAKIX demonstrated statistically significantly greater improvement on the least squares mean change of -3.41 points (95% CI: -5.52, -1.31) from baseline to the end of treatment in final PDSS total score compared to placebo. Study 4 included global assessments, which showed positive trends supporting PDSS total score of improvement.

14.2 Cataplexy in Patients with Narcolepsy

Adult Patients with Narcolepsy

The efficacy of WAKIX for the treatment of cataplexy in adult patients with narcolepsy was evaluated in two multicenter, randomized, double-blind, placebo-controlled studies (Study 3; NCT01800045 and Study 1; NCT01067222). Patients ≥18 years of age who met the International Classification of Sleep Disorders (ICSD-2) criteria for narcolepsy with cataplexy with at least 3 cataplexy attacks per week and an ESS score of ≥12 were eligible to enroll in Study 3; patients meeting the ICSD-2 criteria for narcolepsy (with or without cataplexy) and an ESS score of ≥14 were eligible to enroll in Study 1.

Study 3 included a 7-week treatment period: a 3-week dose titration phase followed by a 4-week stable dose phase. 105 patients were randomized to receive WAKIX or placebo. The dose of WAKIX was initiated at 4.45 mg once daily for the first week, increased to 8.9 mg for the second week, and could remain the same or be decreased or increased at the next two weekly intervals to a maximum of 35.6 mg, based on clinical response and tolerability. No dose adjustments were permitted during the 4-week stable dose phase. 65% of patients reached a stable dose of 35.6 mg. Median age in the study was 37 years and 51% of the patients were male. Race was not collected in this study.

WAKIX demonstrated statistically significantly greater improvement on the primary endpoint, the change in geometric mean number of cataplexy attacks per week from baseline to the average of the 4 week stable dosing period for WAKIX compared to placebo (Table 4).

Study 1 was described in Section 14.1. In the subset of patients with a history of cataplexy (n=49), WAKIX demonstrated statistically significantly greater improvement on the secondary endpoint, the change from baseline in geometric mean daily rate of cataplexy at Week 8 for WAKIX compared to placebo (Table 4).

In both Study 3 and Study 1, examination of demographic subgroups by sex did not suggest differences in response.

Table 4: Efficacy Results for Cataplexy in Adult Patients with Narcolepsy (Study 3 and Study 1)
Study | Endpoint | Treatment Group (N) | Baseline Rate Meana (SD) [95% CI] | Final Rate Meana (SD) [95% CI] | Rate Ratiob (WAKIX to placebo) [95% CI]
Study 3 | Final Mean Weekly Rate of Cataplexy Over 4-Week Stable Dosing Period (primary endpoint) | WAKIX (n=54) | 9.1 (2.0) [7.6, 11.0] | 2.3 (4.4) [1.5, 3.4] | 0.51 [0.44, 0.60]
Study 3 | Final Mean Weekly Rate of Cataplexy Over 4-Week Stable Dosing Period (primary endpoint) | Placebo (n=51) | 7.3 (2.0) [6.0, 8.9] | 4.5 (4.8) [2.9, 7.0] | 0.51 [0.44, 0.60]
Study 1 | Final Mean Daily Rate of Cataplexy at Week 8 (secondary endpoint) | WAKIX (n=25)c | 0.4 (4.0) [0.2, 0.7] | 0.1 (2.8) [0.1, 0.2] | 0.07 [0.01, 0.36]
Study 1 | Final Mean Daily Rate of Cataplexy at Week 8 (secondary endpoint) | Placebo (n=24) c | 0.3 (3.6) [0.1, 0.4] | 0.2 (4.3) [0.1, 0.5] | 0.07 [0.01, 0.36]
CI = confidence interval; SD = standard deviation
a The mean refers to geometric mean, which was used because values for weekly rate of cataplexy were not normally distributed; the geometric mean takes the average of the logs of the individual values and exponentiates that average back to an arithmetic scale.
b The rate ratio is derived from a Poisson regression model.
c Patients with a history of cataplexy.

Pediatric Patients (6 years of age and older) with Narcolepsy

The efficacy of WAKIX for the treatment of cataplexy in pediatric patients 6 years of age and older with narcolepsy was evaluated in one multicenter, randomized, double-blind, placebo-controlled study (Study 4; NCT02611687). Study 4 was described in Section 14.1.

In the subset of patients with a history of cataplexy (n=95), WAKIX demonstrated statistically significantly greater improvement on the least squares mean from baseline to the end of treatment for the average number of cataplexy attacks per week (weekly rate of cataplexy [WRC]) compared with placebo (2.2 in the WAKIX group and 5.6 in the placebo group). The rate ratio, defined as the WRC ratio of the WAKIX group to the placebo group adjusted for baseline value, was 0.39 (95% CI: 0.17; 0.90).

16 HOW SUPPLIED/STORAGE AND HANDLING

16.1 How Supplied

WAKIX (pitolisant) tablets are available as:

4.45 mg: white, round, biconvex film-coated tablet, 3.7 mm diameter, marked with “S” on one side and plain on the other side.

NDC 72028-045-03 – Bottles of 30

17.8 mg: white, round, biconvex film-coated tablet, 7.5 mm diameter, marked with “H” on one side and plain on the other side.

NDC 72028-178-03 – Bottles of 30

16.2 Storage and Handling

Store at 20° C to 25° C (68° F to 77° F); excursions permitted between 15° C to 30° C (59° F to 86° F) [see USP Controlled Room Temperature].

17 PATIENT COUNSELING INFORMATION

Prolongation of the QT Interval

Inform patients to consult their physician immediately if they feel faint, lose consciousness, or have heart palpitations [see Warnings and Precautions (5.1)]. Advise patients to inform their healthcare provider that they are taking WAKIX before any new drug is taken.

Contraception

Advise patients that use of WAKIX may reduce the efficacy of hormonal contraceptives. Advise patients using a hormonal contraceptive to use an alternative non-hormonal contraceptive method of contraception during treatment and for at least 21 days after discontinuing treatment [see Drug Interactions (7.1), Use in Specific Populations (8.3)].

Pregnancy

Advise patients that there is a pregnancy exposure registry that monitors pregnancy outcomes in women exposed to WAKIX during pregnancy [see Use in Specific Populations (8.1)].

Concomitant Medication

Advise patients to inform their healthcare provider if they are taking, or plan to take, any prescription or over-the-counter drugs, because of the potential for interactions between WAKIX and other drugs [see Drug Interactions (7)].

Distributed by: Harmony Biosciences, LLC, Plymouth Meeting, PA 19462 USA

WAKIX is a registered trademark of Bioprojet Europe, Ltd.
Protected by US Patent Numbers 8,207,197 and 8,486,947

Harmony Biosciences name and logo are trademarks of Harmony Biosciences Management, Inc. and are used herein by permission.

Label #100.10